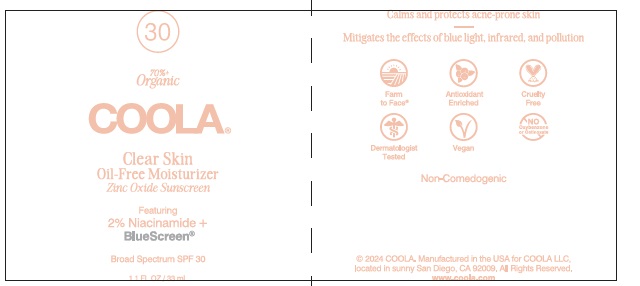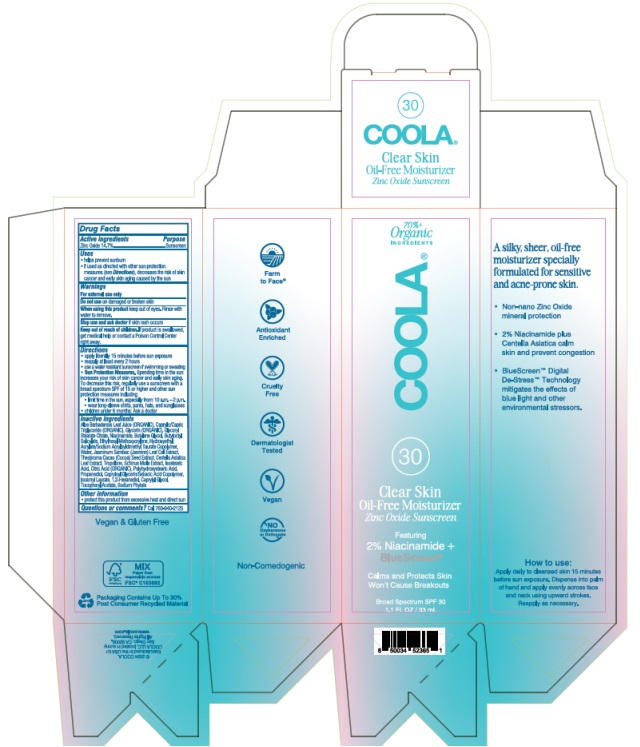 DRUG LABEL: COOLA Clear Skin Oil-Free Moisturizer SPF 30
NDC: 79753-080 | Form: CREAM
Manufacturer: COOLA LLC
Category: otc | Type: HUMAN OTC DRUG LABEL
Date: 20231128

ACTIVE INGREDIENTS: ZINC OXIDE 14.7 g/100 mL
INACTIVE INGREDIENTS: ALOE VERA LEAF; MEDIUM-CHAIN TRIGLYCERIDES; GLYCERIN; GLYCERYL STEARATE CITRATE; NIACINAMIDE; BUTYLENE GLYCOL; BUTYLOCTYL SALICYLATE; ETHYLHEXYL METHOXYCRYLENE; HYDROXYETHYL ACRYLATE/SODIUM ACRYLOYLDIMETHYL TAURATE COPOLYMER (45000 MPA.S AT 1%); WATER; JASMINUM SAMBAC FLOWER; COCOA; CENTELLA ASIATICA LEAF; TROPOLONE; SCHINUS MOLLE FRUITING TOP; ISOSTEARIC ACID; CITRIC ACID MONOHYDRATE; POLYHYDROXYSTEARIC ACID (2300 MW); PROPANEDIOL; CAPRYLOYL GLYCERIN/SEBACIC ACID COPOLYMER (2000 MPA.S); ISOAMYL LAURATE; 1,2-HEXANEDIOL; CAPRYLYL GLYCOL; .ALPHA.-TOCOPHEROL ACETATE; PHYTATE SODIUM

COOLA Clear Skin Oil-Free Moisturizer SPF 30

Drug Facts

Active Ingredients

Zinc Oxide 14.7%

Purpose

Suncreen

INDICATIONS AND USAGE

Uses • helps prevent sunburn • if used as directed with other sun protection measures (see Directions), decreases the risk of skin cancer and early skin aging caused by the sun

Warnings

For external use only

Do not use on damaged or broken skin

When using this product keep out of eyes. Rinse with water to remove.

Stop use and ask doctor if skin rash occurs

Keep out of reach of children. If product is swallowed, get medical help or contact a Poison Control Center right away.

Directions
● apply liberally 15 minutes before sun exposure.
● reapply at least every 2 hours
● use a water resistant sunscreen if swimming or sweating
● Sun Protection Measures. Spending time in the sun
increases your risk of skin cancer and early skin aging.
To decrease this risk, regularly use a sunscreen with a
broad spectrum SPF of 15 or higher and other sun
protection measures including:
● limit time in the sun, especially from: 10 a.m. - 2 p.m.
● wear long-sleeve shirts, pants, hats, and sunglasses
●Children under 6 months: Ask a doctor

Inactive Ingredients

Aloe Barbadensis Leaf Juice (ORGANIC), Caprylic/Capric
Triglyceride (ORGANIC), Glycerin (ORGANIC), Glyceryl
Stearate Citrate, Niacinamide, Butylene Glycol, Butyloctyl
Salicylate, Ethylhexyl Methoxycrylene, Hydroxyethyl
Acrylate/Sodium Acryloyldimethyl Taurate Copolymer,
Water, Jasminum Sambac (Jasmine) Leaf Cell Extract,
Theobroma Cacao (Cocoa) Seed Extract, Centella Asiatica
Leaf Extract, Tropolone, Schinus Molle Extract, Isostearic
Acid, Citric Acid (ORGANIC), Polyhydroxystearic Acid,
Propanediol, Capryloyl Glycerin/Sebacic Acid Copolymer,
Isoamyl Laurate, 1,2-Hexanediol, Caprylyl Glycol,
Tocopheryl Acetate, Sodium Phytate

Other information

- protect this product from excessive heat and direct sun

Questions or comments?
Call 760-940-2125

COOLA Clear Skin Oil-Free Moisturizer SPF 30 Label

COOLA

Clear Skin

Oil-Free Moisturizer

Zinc Oxide Sunscreen

Broad Spectrum SPF 30

1.1 FL OZ / 33 mL

© 2024 COOLA

Manufactured in the USA for

COOLA LLC, locatedin sunny

San Diego, CA 92009.

All Rights Reserved.

www.coola.com

res